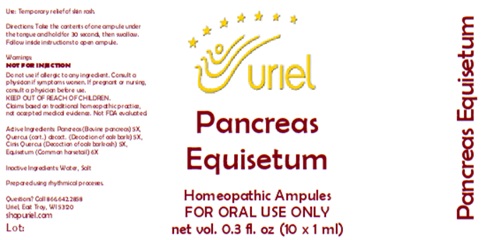 DRUG LABEL: Pancreas Equisetum
NDC: 48951-8002 | Form: LIQUID
Manufacturer: Uriel Pharmacy Inc.
Category: homeopathic | Type: HUMAN OTC DRUG LABEL
Date: 20260203

ACTIVE INGREDIENTS: SUS SCROFA PANCREAS 5 [hp_X]/1 mL; QUERCUS ROBUR WHOLE 5 [hp_X]/1 mL; EQUISETUM ARVENSE TOP 6 [hp_X]/1 mL
INACTIVE INGREDIENTS: WATER; SODIUM CHLORIDE

Pancreas Equisetum

PURPOSE

Use: Temporary relief of skin rash.

INDICATIONS AND USAGE

FOR ORAL USE ONLY

DOSAGE AND ADMINISTRATION

Directions: Take the contents of one ampule under the tongue and hold for 30 seconds, then swallow. Follow inside instructions to open ampule.

Warnings:
NOT FOR INJECTION
Do not use if allergic to any ingredient. Consult a physician if symptoms worsen. If pregnant or nursing, consult a physician before use.
Claims based on traditional homeopathic practice, not accepted medical evidence. Not FDA evaluated.

KEEP OUT OF REACH OF CHILDREN.

ACTIVE INGREDIENT

Active Ingredients: Pancreas (Bovine pancreas) 5X, Quercus (cort.) decoct. (Decoction of oak bark) 5X, Cinis Quercus (Decoction of oak bark ash) 5X, Equisetum (Common horsetail) 6X

Inactive Ingredients: Water, Salt

Prepared using rhythmical processes.

QUESTIONS

Questions? Call 866.642.2858 Uriel, East Troy, WI 53120 shopuriel.com Lot: